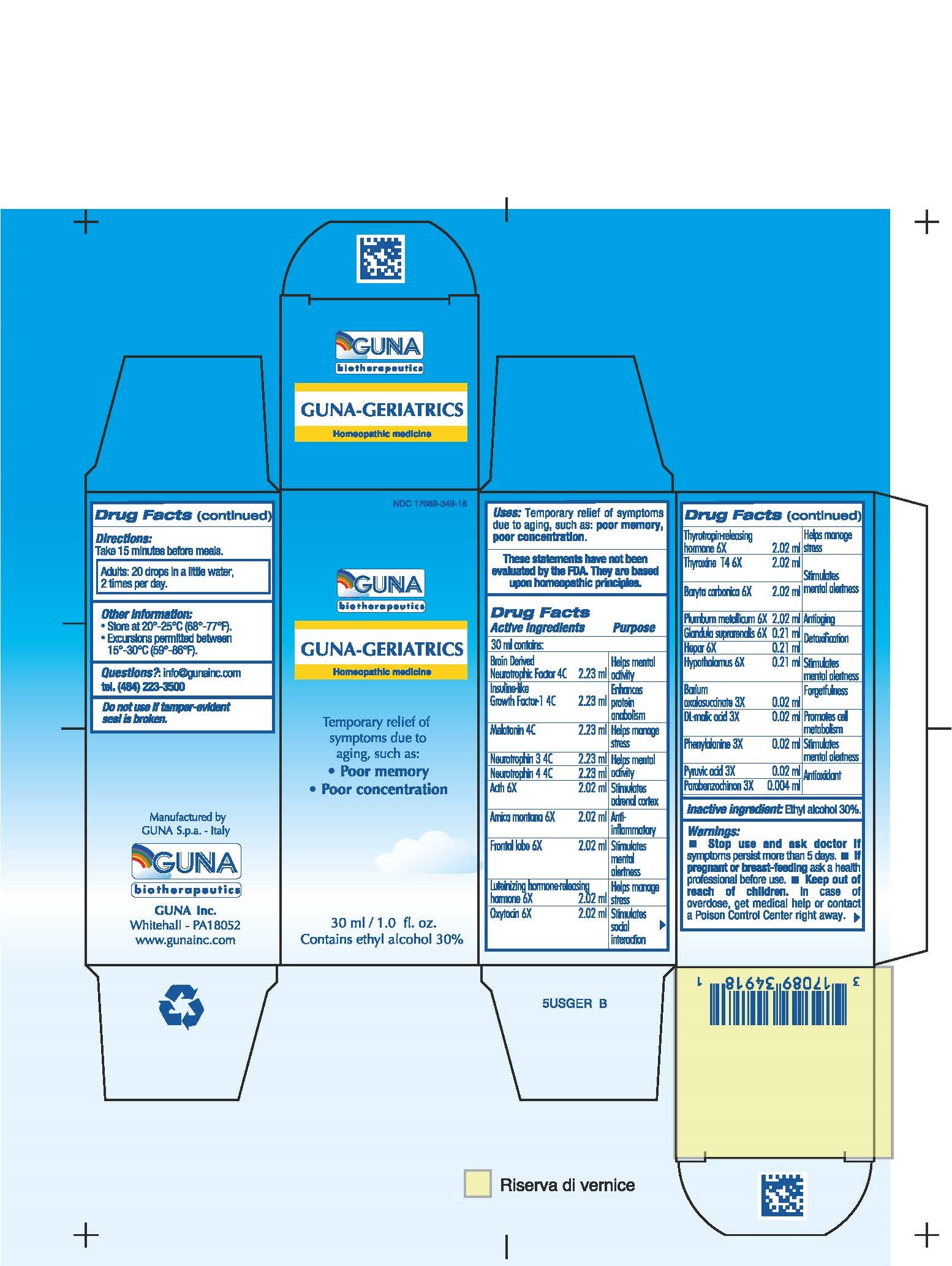 DRUG LABEL: GUNA-GERIATRICS
NDC: 17089-349 | Form: SOLUTION/ DROPS
Manufacturer: Guna spa
Category: homeopathic | Type: HUMAN OTC DRUG LABEL
Date: 20181222

ACTIVE INGREDIENTS: QUINONE 3 [hp_X]/30 mL; BARIUM OXALOSUCCINATE 3 [hp_X]/30 mL; CORTICOTROPIN 6 [hp_X]/30 mL; ARNICA MONTANA 6 [hp_X]/30 mL; BARIUM CARBONATE 6 [hp_X]/30 mL; BRAIN-DERIVED NEUROTROPHIC FACTOR HUMAN 4 [hp_C]/30 mL; MALIC ACID 3 [hp_X]/30 mL; SUS SCROFA FRONTAL LOBE 6 [hp_X]/30 mL; SUS SCROFA ADRENAL GLAND 6 [hp_X]/30 mL; PORK LIVER 6 [hp_X]/30 mL; SUS SCROFA HYPOTHALAMUS 6 [hp_X]/30 mL; RINFABATE 4 [hp_C]/30 mL; LUTRELIN 6 [hp_X]/30 mL; MELATONIN 4 [hp_C]/30 mL; NEUROTROPHIN-3 4 [hp_C]/30 mL; NEUROTROPHIN-4 4 [hp_C]/30 mL; OXYTOCIN 6 [hp_X]/30 mL; PHENYLALANINE 3 [hp_X]/30 mL; LEAD 6 [hp_X]/30 mL; PYRUVIC ACID 3 [hp_X]/30 mL; THYROTROPIN ALFA 6 [hp_X]/30 mL; LEVOTHYROXINE 6 [hp_X]/30 mL
INACTIVE INGREDIENTS: ALCOHOL

GUNA-GERIATRICS

ACTIVE INGREDIENTS/PURPOSE

ACTH 6X ADRENAL SUPPORT
ARNICA MONTANA 6X ANTI-INFLAMMATORY
BARIUM OXALOSUCCINATE 3X FORGETFULNESS
BARYTA CARBONICA 6X IMPROVES MENTAL ATTENTION
BRAIN DERIVED NEUROTROPHIC FACTOR 4C HELPS MENTAL ACTIVITY
DL-MALIC ACID 3X PROMOTE CELL METABOLISM
FRONTAL LOBE 6X STIMULATES MENTAL ALERTNESS
GLANDULA SUPRARENALIS 6X DETOXIFICATION
HEPAR 6X DETOXIFICATION
HYPOTHALAMUS 6X IMPROVES MENTAL ATTENTION
INSULINE-LIKE GROWTH FACTOR-1 4C ENHANCES PROTEIN ANABOLISM
LUTEINIZING HORMONE-RELEASING HORMONE 6X HELPS MANAGE STRESS
MELATONIN 4C HELPS MANAGE STRESS
NEUROTROPHIN 3 4C HELPS MENTAL ACTIVITY
NEUROTROPHIN 4 4C HELPS MENTAL ACTIVITY
OXYTOCIN 6X STIMULATES SOCIAL RECOGNITION
PARABENZOCHINON 3X ANTIOXIDANT
PHENYLALANINE 3X STIMULATES MENTAL ALERTNESS
PLUMBUM METALLICUM 6X ANTIAGING
PYRUVIC ACID 3X ANTIOXIDANT
THYROTROPIN-RELEASING HORMONE 6X HELPS MANAGE STRESS
THYROXINE T4 6X STIMULATES MENTAL ALERTNESS

USES

TAKE 15 MINUTES BEFORE MEALS

WARNINGS

- Stop use and ask doctor if symptoms persist more than 5 days.
- If pregnant or breast-feeding ask a health professional before use.
- Keep out of reach of children. In case of overdose, get medical help or contact a Poison Control Center right away.
- Contains ethyl alcohol 30%

PREGNANCY

If pregnant or breast-feeding ask a doctor before use

WARNINGS

Keep this and all medicines out of reach of children

DIRECTIONS

Take 15 minutes before meals
Adults : 20 drops in a little water, 2 times per day

QUESTIONS

Questions?: info@gunainc.com, tel. (484) 223-3500

- Inactive ingredient: Ethyl alcohol 30%.

PURPOSE

For the temporary relief symptoms due to aging, scuh as:

- poor memory
- impaired concentration